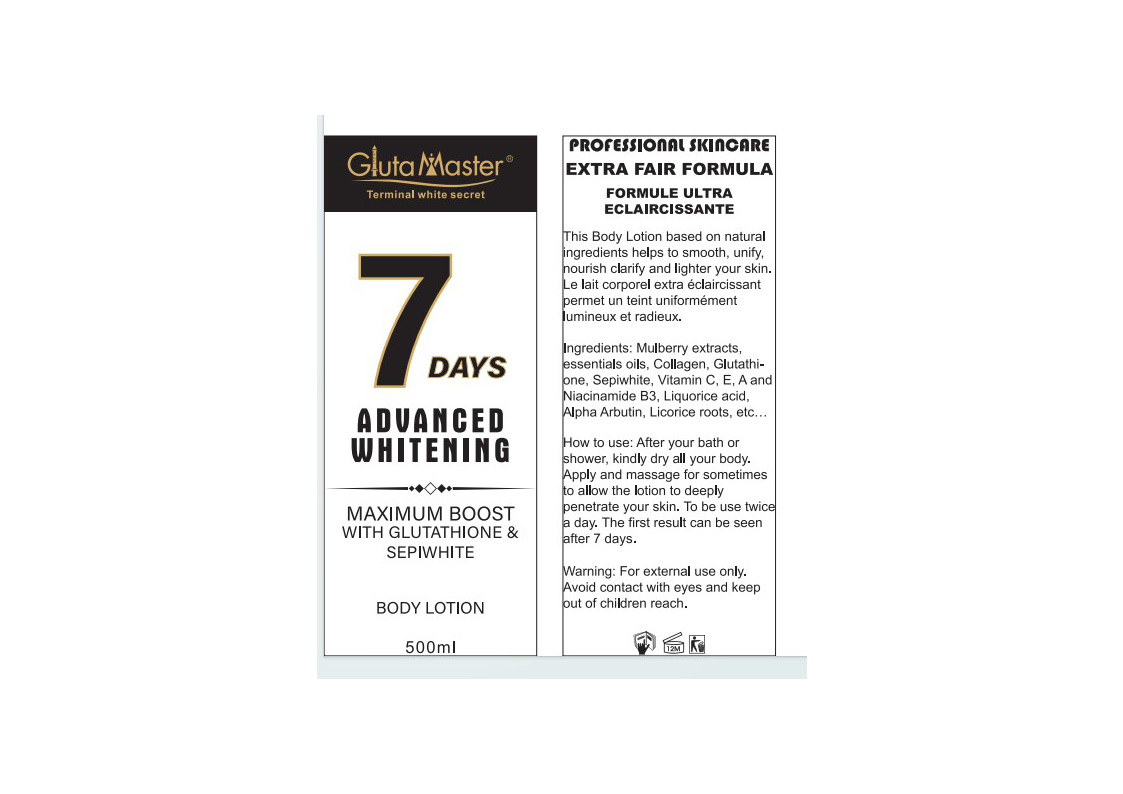 DRUG LABEL: 7Days Advanced Whitening BodyLotion
NDC: 84423-032 | Form: EMULSION
Manufacturer: Guangzhou Kadiya Biotechnology Co., Ltd.
Category: otc | Type: HUMAN OTC DRUG LABEL
Date: 20240825

ACTIVE INGREDIENTS: KOJIC ACID 5 mg/500 mL; GLUTATHIONE 4 mg/500 mL; NIACINAMIDE 11.5 mg/500 mL
INACTIVE INGREDIENTS: UREA; DMDM HYDANTOIN; FD&C YELLOW NO. 5; FD&C BLUE NO. 1; CETOSTEARYL ALCOHOL; DIMETHICONE; MINERAL OIL; POLYOXYL 20 CETOSTEARYL ETHER; PEG-100 STEARATE; TROLAMINE; CARBOMER HOMOPOLYMER, UNSPECIFIED TYPE; C13-16 ISOPARAFFIN; ALLANTOIN; BUTYLENE GLYCOL; AMARANTH; METHYLPARABEN; SODIUM CHLORIDE; WATER; GLYCERIN; GLYCERYL MONOSTEARATE; IODOPROPYNYL BUTYLCARBAMATE; POTASSIUM CETYL PHOSPHATE; 3-O-ETHYL ASCORBIC ACID; EDETATE DISODIUM; PONCEAU 4R; FD&C YELLOW NO. 6; PROPYLPARABEN; XANTHAN GUM

PURPOSE

Used for skin whitening

INACTIVE INGREDIENT

AQUA、MINERAL OIL、GLYCERIN、CETEARYL ALCOHOL、UREA、DIMETHICONE、GLYCERYL STEARATE、CETEARETH-20、PEG-100 STEARATE、POTASSIUM CETYL、PHOSPHATE、DMDM HYDANTOIN、TRIETHANOLAMINE、ALLANTOIN、CARBOMER、AROMA、METHYLPARABEN、C13-16 ISOPARAFFIN、PROPYLPARABEN、XANTHAN GUM、3-o-ETHYL ASCORBIC ACID、DISODIUM EDTA、CI 19140、BUTYLENE GLYCOL、IODOPROPYNYL BUTYLCARBAMATE、CI 16255、SODIUM、CHLORIDE、CI 16185、CI 15985、CI 42090

WARNINGS

1.Before use, perform a skin test on your arm and discontinue use if you have allergy symptoms or skin abnormalities.
2、For external use only, avoid contact with eyes when used
3、Keep out of reach of children

INDICATIONS AND USAGE

How to use: After your bath or shower, kindly dry all your body. Apply and massage for sometimes to allow the lotion to deeply penetrate your skin

DOSAGE AND ADMINISTRATION

To be use twice a day. The first result can be seen after 7 days.

KEEP OUT OF REACH OF CHILDREN SECTION

Active Ingredients
NIACINAMIDE2.3%
GLUTATHIONE0.8%
KOJIC ACID 1%
HYDROLYZED COLLAGEN EXTRACT2%

PACKAGE LABEL

Active Ingredients
NIACINAMIDE2.3%
GLUTATHIONE0.8%
KOJIC ACID 1%
HYDROLYZED COLLAGEN EXTRACT2%

Uses：
Used for skin whitening
The storage method：
Store sealed in a cool place and out of sunlight

Warning.
1.Before use, perform a skin test on your arm and discontinue use if you have allergy symptoms or skin abnormalities.
2、For external use only, avoid contact with eyes when used
3、Keep out of reach of children

Inactive ingredients：
AQUA、MINERAL OIL、GLYCERIN、CETEARYL ALCOHOL、UREA、DIMETHICONE、GLYCERYL STEARATE、CETEARETH-20、PEG-100 STEARATE、POTASSIUM CETYL、PHOSPHATE、DMDM HYDANTOIN、TRIETHANOLAMINE、ALLANTOIN、CARBOMER、AROMA、METHYLPARABEN、C13-16 ISOPARAFFIN、PROPYLPARABEN、XANTHAN GUM、3-o-ETHYL ASCORBIC ACID、DISODIUM EDTA、CI 19140、BUTYLENE GLYCOL、IODOPROPYNYL BUTYLCARBAMATE、CI 16255、SODIUM、CHLORIDE、CI 16185、CI 15985、CI 42090